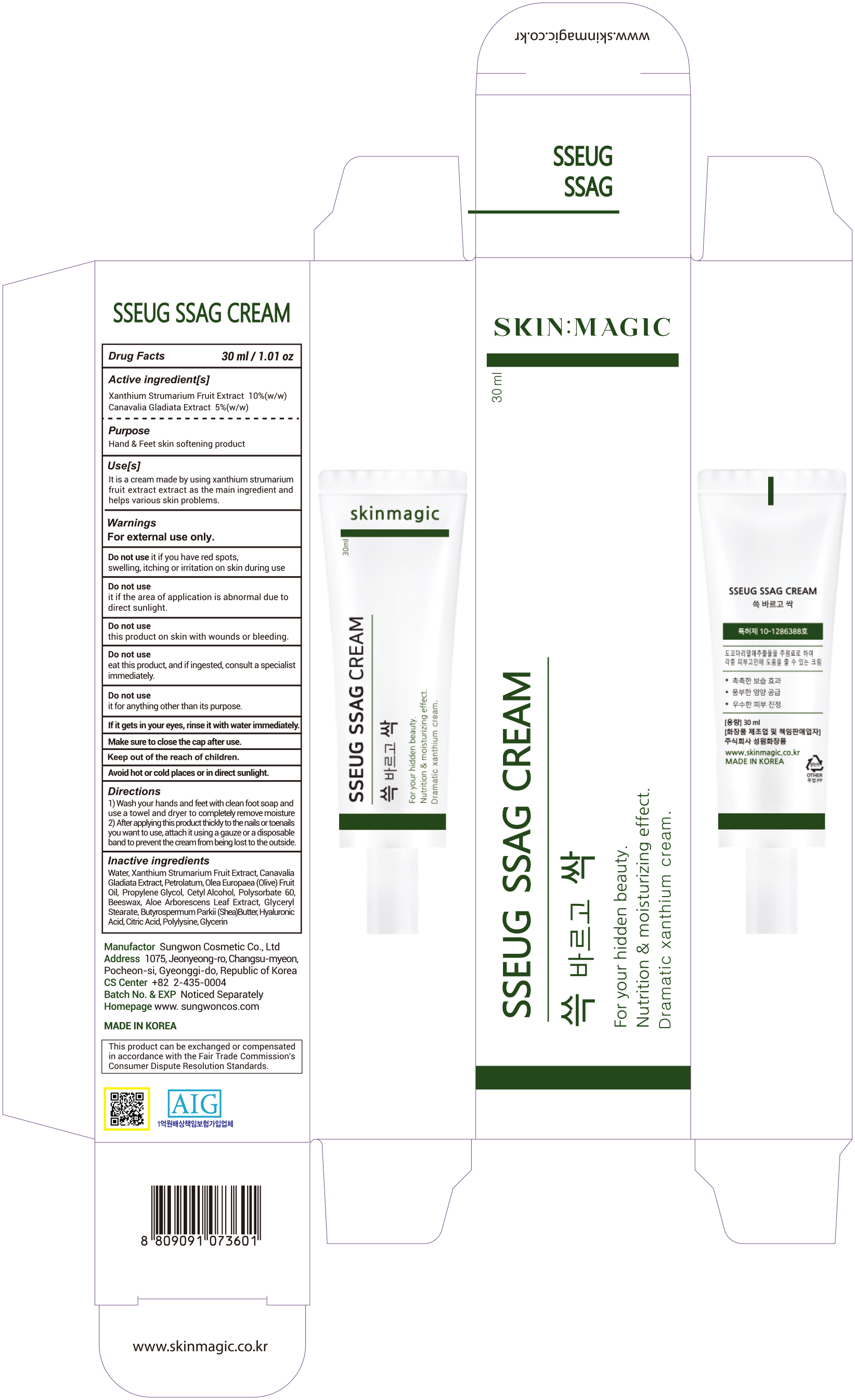 DRUG LABEL: SSEUG SSAGCREAM
NDC: 74721-0100 | Form: CREAM
Manufacturer: S-ONE PHARMACEUTICAL INC
Category: otc | Type: HUMAN OTC DRUG LABEL
Date: 20230102

ACTIVE INGREDIENTS: CANAVALIA GLADIATA WHOLE 5 g/100 mL; XANTHIUM STRUMARIUM FRUIT 10 g/100 mL
INACTIVE INGREDIENTS: PETROLATUM; CETYL ALCOHOL; SHEA BUTTER; GLYCERIN; OLIVE OIL; PROPYLENE GLYCOL; GLYCERYL STEARATE SE; CITRIC ACID MONOHYDRATE; POLYSORBATE 60; YELLOW WAX; ALOE VERA LEAF; HYALURONIC ACID; WATER; POLY-L-LYSINE (30000-70000 MW)

74721-0100 SSEUG SSAG CREAM

Active ingredients

- Xanthium Strumarium Fruit Extract 10%(w/w)
- Canavalia Gladiata Extract 5%(w/w)

Purpose

Hand & Feet skin softening product

Use

It is a cream made by using xanthium strumarium fruit extract
as the main ingredient and helps various skin problems.

Warnings

For external use only.

Make sure to close the cap after use.

Do not use it if you have red spots,
swelling, itching or irritation on skin during use

Do not use it if the area of application is abnormal
due to direct sunlight.

Do not use this product on skin with wounds or bleeding.

Do not use eat this product, and if ingested,
consult a specialist immediately.

Do not use it for anything other than its purpose.

If it gets in your eyes, rinse it with water immediately.

Keep out of the reach of children.

Other Information

Avoid hot or cold places or in direct sunlight.

Directions

1) Wash your hands and feet with clean foot soap and
use a towel and dryer to completely remove moisture
2) After applying this product thickly to the nails or toenails
you want to use, attach it using a gauze or a disposable
band to prevent the cream from being lost to the outside.

Inactive ingredients

Water, Petrolatum, Olea Europaea (Olive) Fruit Oil, Propylene Glycol, Cetyl Alcohol, Polysorbate 60,
Beeswax, Aloe Arborescens Leaf Extract, Glyceryl Stearate, Butyrospermum Parkii (Shea)Butter,
Hyaluronic Acid, Citric Acid, Polylysine, Glycerin